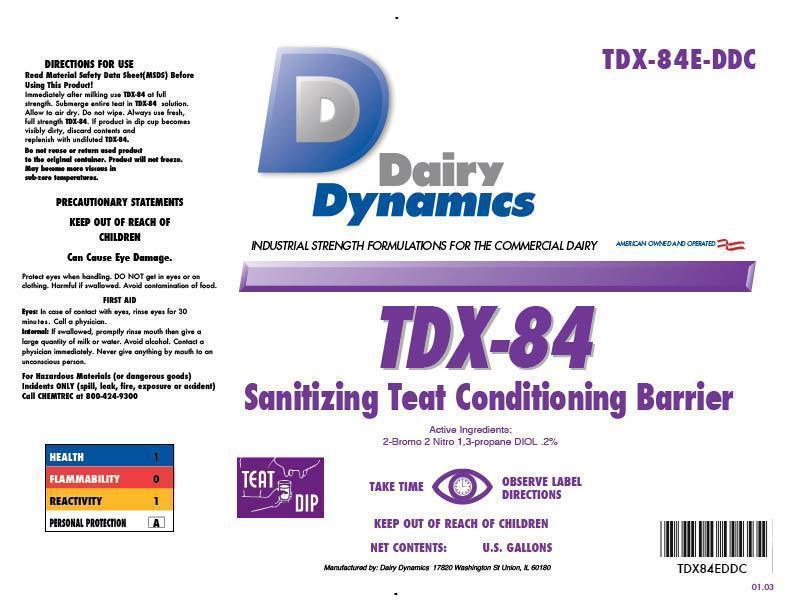 DRUG LABEL: TDX-84
NDC: 67351-984 | Form: SOLUTION
Manufacturer: Dairy Dynamics L.L.C.
Category: animal | Type: OTC ANIMAL DRUG LABEL
Date: 20150114

ACTIVE INGREDIENTS: BRONOPOL 0.3 g/1 L
INACTIVE INGREDIENTS: WATER; FD&C YELLOW NO. 6; C9-11 PARETH-3; CITRIC ACID MONOHYDRATE; PROPYLENE GLYCOL; GLYCERIN; XANTHAN GUM; PHENOXYETHANOL

TDX-84
Sanitizing Teat Conditioning Barrier

WARNINGS AND PRECAUTIONS

Dairy Dynamics

INDUSTRIAL STRENGTH FORMULATIONS FOR THE COMMERCIAL DAIRY

AMERICAN OWNED AND OPERATED

TDX-84

Sanitizing Teat Conditioning Barrier

DIRECTIONS FOR USE

Read Material Safety Data Sheet (MSDS) Before Using This Product!

Immediately after milking use TDX-84 at full strength. Submerge entire teat in TDX-84 solution. Allow to air dry. Do not wipe. Always use fresh full strength TDX-84. If product in dip cup becomes visibly dirty, discard contents and replenish with undiluted TDX-84.

Do not reuse or return used product to the original container. Product will not freeze. May become more viscous in sub-zero temperatures.

PRECAUTIONS

PRECAUTIONARY STATEMENTS

KEEP OUT OF REACH OF CHILDREN

Can Cause Eye Damage.

Protect eyes when handling. DO NOT get in eyes or on clothing. Harmful if swallowed. Avoid contamination of food.

FIRST AID

Eyes: in case of contact with eyes, rinse eyes for 30 minutes. Call a physician.

Internal: if swallowed, promptly rinse mouth then give a large quantity of milk or water. Avoid alcohol. Contact a physician immediately. Never give anything by mouth to an unconscious person.

For Hazardous Materials (or dangerous goods) Incidents ONLY (spill, leak, fire, exposure or accident) Call CHEMTREC at 800-424-9300

HEALTH 1

FLAMMABILITY 0

REACTIVITY 1

PERSONAL PROTECTION A

ACTIVE INGREDIENT

Active Ingredients: 2-Bromo 2 Nitro 1,3-propane DIOL .2%

TEAT DIP

TAKE TIME OBSERVE LABEL DIRECTIONS

KEEP OUT OF REACH OF CHILDREN

NET CONTANTS: U.S. GALLONS

Manufactured by: Dairy Dynamics 17820 Washington St Union, IL 60180

TDX-84E-DDC

TDX84EDDC